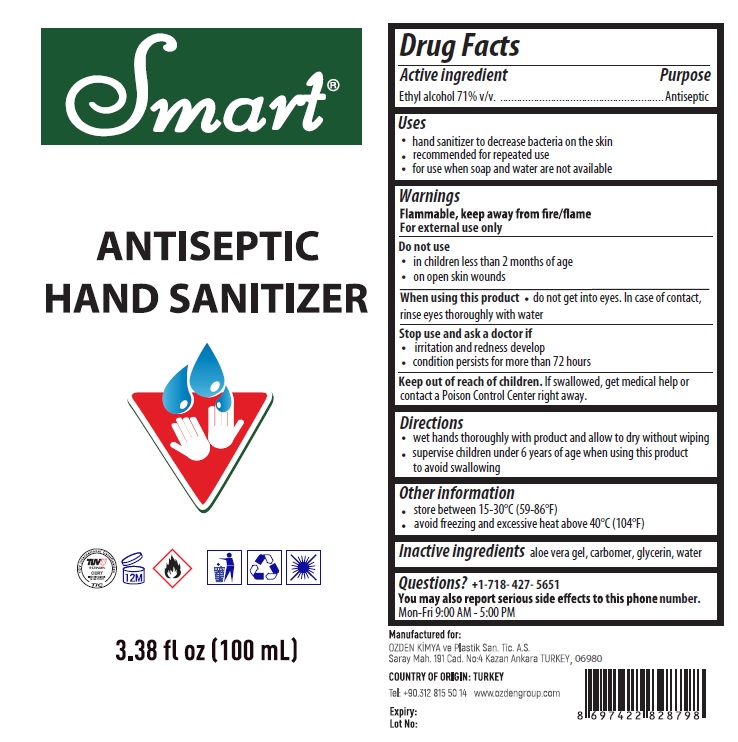 DRUG LABEL: Smart ANTISEPTIC HAND SANITIZER
NDC: 78826-100 | Form: GEL
Manufacturer: OZDEN KIMYA VE PLASTIK SANAYI TICARET ANONIM SIRKETI
Category: otc | Type: HUMAN OTC DRUG LABEL
Date: 20200628

ACTIVE INGREDIENTS: ALCOHOL 71 mL/100 mL
INACTIVE INGREDIENTS: ALOE VERA LEAF; CARBOMER HOMOPOLYMER, UNSPECIFIED TYPE; GLYCERIN; WATER

Smart® ANTISEPTIC HAND SANITIZER

Active ingredient

Ethyl alcohol 71% v/v

Purpose

Antiseptic

Uses

- hand sanitizer to decrease bacteria on the skin
- recommended for repeated use
- for use when soap and water are not available

Warnings

Flammable, keep away from fire/flame

For external use only

Do not use

- in children less than 2 months of age
- on open skin wounds

When using this product • do not get into eyes. In case of contact, rinse eyes thoroughly with water

Stop use and ask a doctor if

- irritation and redness develop
- condition persists for more than 72 hours

Keep out of reach of children. If swallowed, get medical help or contact a Poison Control Center right away.

Directions

- wet hands thoroughly with product and allow to dry without wiping
- supervise children under 6 years of age when using this product to avoid swallowing

Other information

- store between 15-30°C (59-86°F)
- avoid freezing and excessive heat above 40°C (104°F)

Inactive ingredients

aloe vera gel, carbomer, glycerin, water

Questions?

+1-718- 427- 5651

You may also report serious side effects to this phone number.

Mon-Fri 9:00 AM - 5:00 PM

Manufactured for:

OZDEN KIMYA ve Plastik San. Tic. A.S.

Saray Mah. 191 Cad. No:4, Kazan, Ankara, TURKEY, 06980

COUNTRY OF ORIGIN: TURKEY

Tel: +90.312 815 50 14 www.ozdengroup.com